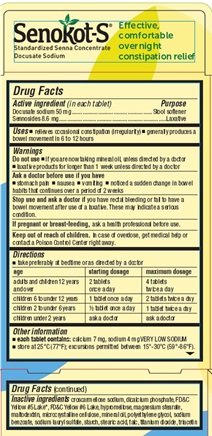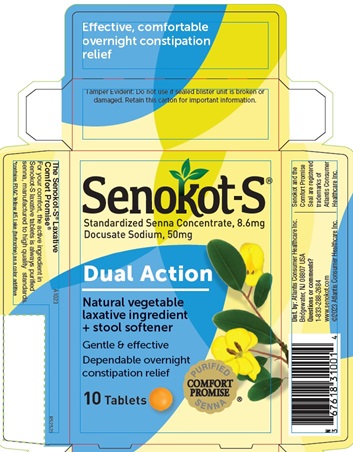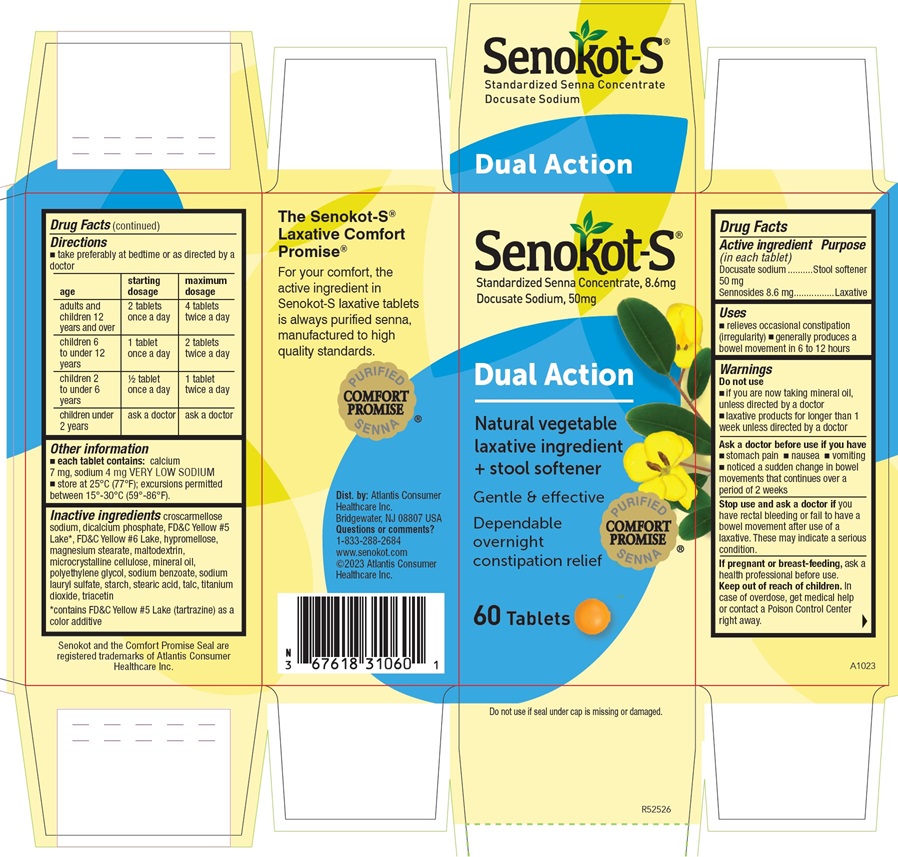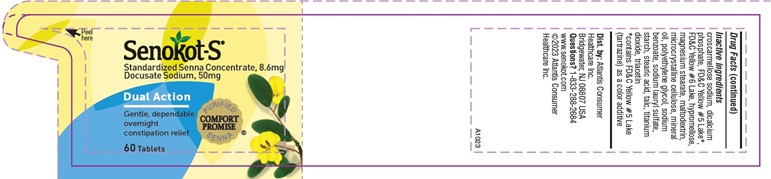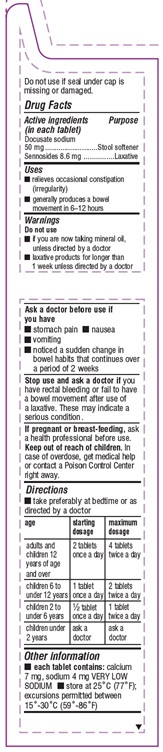 DRUG LABEL: Senokot-S
NDC: 67618-310 | Form: TABLET
Manufacturer: Atlantis Consumer Healthcare, Inc.
Category: otc | Type: HUMAN OTC DRUG LABEL
Date: 20251229

ACTIVE INGREDIENTS: SENNOSIDES 8.6 mg/1 1; DOCUSATE SODIUM 50 mg/1 1
INACTIVE INGREDIENTS: CROSCARMELLOSE SODIUM; CALCIUM PHOSPHATE, DIBASIC, ANHYDROUS; FD&C YELLOW NO. 5; FD&C YELLOW NO. 6; HYPROMELLOSE, UNSPECIFIED; MAGNESIUM STEARATE; MALTODEXTRIN; CELLULOSE, MICROCRYSTALLINE; MINERAL OIL; POLYETHYLENE GLYCOL, UNSPECIFIED; SODIUM BENZOATE; SODIUM LAURYL SULFATE; STARCH, CORN; STEARIC ACID; TALC; TITANIUM DIOXIDE; TRIACETIN

Senokot-S
(standardizedsenna concentrate and docusate sodium)

Drug Facts

Active ingredients (in each tablet)

Docusate sodium         50mg

Sennosides                      8.6mg

Purpose

Stool softener

Laxative

Uses

- relieves occasional constipation (irregularity)
- generally produces a bowel movement in 6-12 hours

Warnings

Do not use

- if you are now taking mineral oil, unless directed by adoctor
- laxative products for longer than 1 week unless directedby a doctor

Ask a doctor before use if you have

- stomach pain
- nausea
- vomiting
- noticed a sudden change in bowel habits that continues overa period of 2 weeks

STOP USE

Stop using and ask a doctor if youhave rectal bleeding or fail to have a bowel movement after use ofa laxative. These may indicate a serious condition.

PREGNANCY OR BREAST FEEDING

If pregnant or breast-feeding, ask a health professional before use.

Keep out of reachof children.

In case ofoverdose, get medical help or contact a Poison Control Center rightaway.

Directions

- take preferably at bedtime or as directed by a doctor

age | startingdosage | maximumdosage
adults and children 12 years of age and over | 2 tablets oncea day | 4 tablets twicea day
children 6 to under 12 years | 1 tablet once a day | 2 tablets twice a day
children 2 to under 6 years | 1/2 tablet once a day | 1 tablet twice a day
children under 2 years | ask a doctor | ask a doctor

Other information

- each tablet contains: calcium 7 mg, sodium 4 mg VERYLOW SODIUM
- store at 25°C (77°F); excursions permitted between 15°-30°C(59°-86°F)

Inactive ingredients

Inactive ingredients croscarmellose sodium, dicalcium phosphate, FD&C Yellow#5 Lake*, FD&C Yellow #6 Lake, hypromellose, magnesium stearate,maltodextrin, microcrystalline cellulose, mineral oil, polyethyleneglycol, sodium benzoate, sodium lauryl sulfate, starch, stearic acid,talc, titanium dioxide, triacetin

©2020

Avrio Health L.P.

A1023

Senokot-S 60 Tablets Label
NDC: 67618-310-60

Senokot-S 60 Tablets Leaflet
NDC: 67618-310-60

Senokot-S 60 Tablets Carton
NDC: 67618-310-60

Senokot-S 10 Tablets Carton
NDC: 67618-310-01